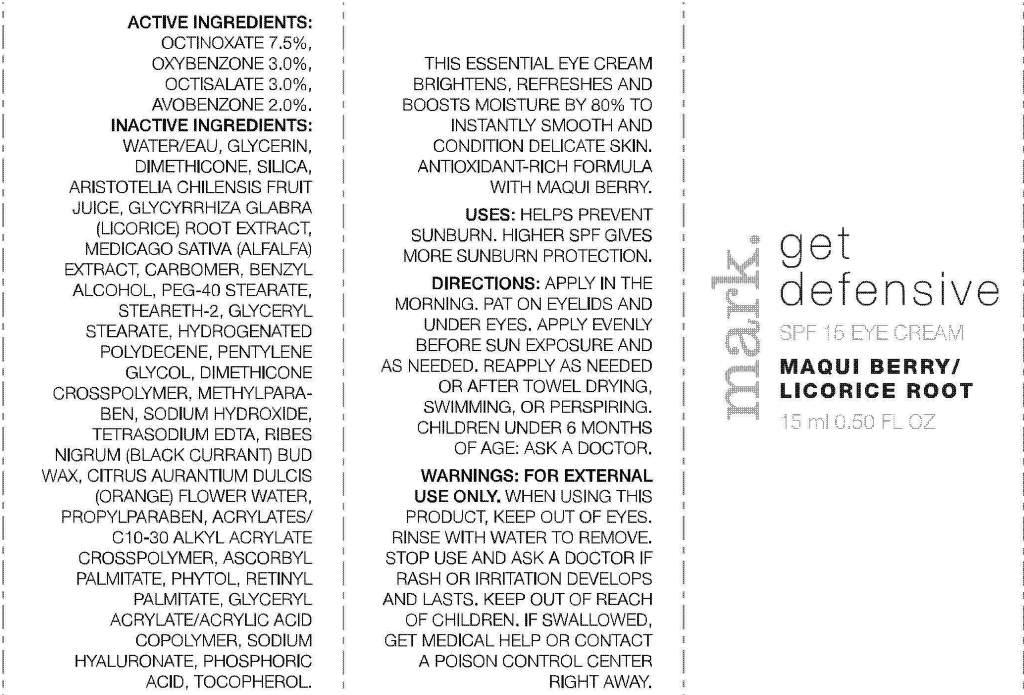 DRUG LABEL: mark.
NDC: 10096-0255 | Form: CREAM
Manufacturer: Avon Products, Inc.
Category: otc | Type: HUMAN OTC DRUG LABEL
Date: 20110414

ACTIVE INGREDIENTS: OCTINOXATE 1.125 mL/15 mL; OXYBENZONE 0.45 mL/15 mL; OCTISALATE 0.45 mL/15 mL; AVOBENZONE 0.3 mL/15 mL

INDICATIONS AND USAGE

USES: HELPS PREVENT SUNBURN. HIGHER SPF GIVES MORE SUNBURN PROTECTION.

DOSAGE AND ADMINISTRATION

DIRECTIONS: APPLY IN THE MORNING. PAT ON EYELIDS AND UNDER EYES. APPLY EVENLY BEFORE SUN EXPOSURE AND AS NEEDED. REAPPLY AS NEEDED OR AFTER TOWEL DRYING, SWIMMING, OR PERSPIRING. CHILDREN UNDER 6 MONTHS OF AGE: ASK A DOCTOR.

WARNINGS

WARNINGS: FOR EXTERNAL USE ONLY. WHEN USING THIS PRODUCT, KEEP OUT OF EYES. RINSE WITH WATER TO REMOVE. STOP USE AND ASK A DOCTOR IF RASH OR IRRITATION DEVELOPS AND LASTS. KEEP OUT OF REACH OF CHILDREN. IF SWALLOWED, GET MEDICAL HELP OR CONTACT A POISON CONTROL CENTER RIGHT AWAY.

ACTIVE INGREDIENTS:
OCTINOXATE 7.5%
OXYBENZONE 3.0%
OCTISALATE 3.0%
AVOBENZONE 2.0%

INACTIVE INGREDIENTS:

WATER/EAU
GLYCERIN
DIMETHICONE
SILICA
ARISTOTELIA CHILENSIS FRUIT JUICE
GLYCYRRHIZA GLABRA (LICORICE) ROOT EXTRACT
MEDICAGO SATIVA (ALFALFA) EXTRACT
CARBOMER
BENZYL ALCOHOL
PEG-40 STEARATE
STEARETH-2
GLYCERYL STEARATE
HYDROGENATED POLYDECENE
PENTYLENE GLYCOL
DIMETHICONE CROSSPOLYMER
METHYLPARABEN
SODIUM HYDROXIDE
TETRASODIUM EDTA
RIBES NIGRUM (BLACK CURRANT) BUD WAX
CITRUS AURANTIUM DULCIS (ORANGE) FLOWER WATER
PROPYLPARABEN
ACRYLATES/C10-30 ALKYL ACRYLATE CROSSPOLYMER
ASCORBYL PALMITATE
PHYTOL
RETINYL PALMITATE
GLYCERYL ACRYLATE/ACRYLIC ACID COPOLYMER
SODIUM HYALURONATE
PHOSPHORIC ACID
TOCOPHEROL